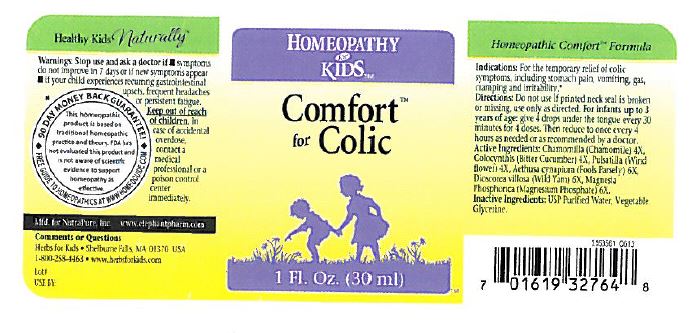 DRUG LABEL: Comfort for Colic
NDC: 64616-116 | Form: LIQUID
Manufacturer: Vitality Works, Inc.
Category: homeopathic | Type: HUMAN OTC DRUG LABEL
Date: 20251217

ACTIVE INGREDIENTS: PULSATILLA PRATENSIS 4 [hp_X]/0.05 mL; AETHUSA CYNAPIUM 4 [hp_X]/0.05 mL; DIOSCOREA VILLOSA TUBER 6 [hp_X]/0.05 mL; MAGNESIUM PHOSPHATE, DIBASIC 6 [hp_X]/0.05 mL; CHAMOMILE 4 [hp_X]/0.05 mL; CITRULLUS COLOCYNTHIS FRUIT 4 [hp_X]/0.05 mL
INACTIVE INGREDIENTS: WATER; GLYCERIN

Comfort for Colic

Indications

For the temporary relief of colic symptoms, including stomach pain, vomiting, gas, cramping and irritability.

PURPOSE

For the temporary relief of colic symptoms, including stomach pain, vomiting, gas, cramping and irritability

Directions

Do not use if printed neck seal is broken or missing, use only as directed. For infants up to 3 years of age: give 4 dropsunder the tongue every 30 minutes for 4 doses. Then reduce to once every 4 hours as needed or recommended by a doctor.

Active Ingredients

Chamomilla (Chamomile) 4X, Colocynthsis (Bitter cucumber) 4X, Pulsatilla (Wind flower) 4X, Aethusa cynapium (Fools parsley) 6x, Dioscorea villosa (wild yam) 6X, Magnesia Phosphorica (Magensium phophate) 6X

Inactive ingredients

USP Purified water, Vegetable glycerin

Warnings

Stop use and ask a doctor if

symptoms do not improve in 7 days or if new symptoms appear

if your child experiences recurring gastrointestinal upsets, frequent headaches or persistent fatigue

Keep out of reach of children. In case of accidental overdose, contact a medical professional or a poison control center immediately.

Comments or Questions

Health for Kids Shelbourne Falls, MA 01370 USA

1-800-255-4463

www.herbsforkids.com